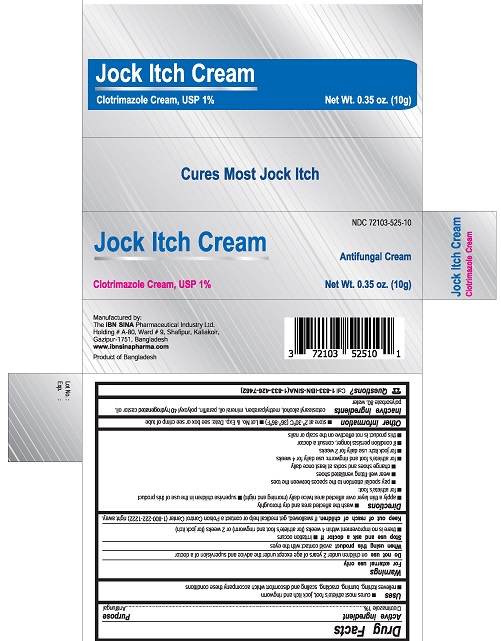 DRUG LABEL: Jock Itch
NDC: 72103-525 | Form: CREAM
Manufacturer: The IBN SINA Pharmaceutical Industry Ltd.
Category: otc | Type: HUMAN OTC DRUG LABEL
Date: 20190314

ACTIVE INGREDIENTS: CLOTRIMAZOLE 1 g/100 g
INACTIVE INGREDIENTS: METHYLPARABEN; MINERAL OIL; PARAFFIN; POLYOXYL 40 HYDROGENATED CASTOR OIL; POLYSORBATE 80; CETOSTEARYL ALCOHOL; WATER

Jock Itch Cream

Drug Facts

Active ingredient

Clotrimazole 1%

Purpose

Antifungal

Uses

- cures most athlete's foot, jock itch and ringworm
- relieves itching, burning, cracking, scaling and discomfort which accompany these conditions

Warnings

For external use only

Do not use on children under 2 years of age except under the advice and supervision of a doctor

When using this product avoid contact with the eyes

Stop use and ask a doctor if

- irritation occurs
- there is no improvement within 4 weeks (for athlete's foot and ringworm) or 2 weeks (for jock itch)

Keep out of reach of children. If swallowed, get medical help or contact a Poison Control Center (1-800-222-1222) right away.

Directions

- wash the affected area and dry thoroughly
- apply a thin layer over affected area twice daily (morning and night)
- supervise children in the use of this product
- for athlete's foot:
- pay special attention to the spaces between the toes
- wear well-fitting ventilated shoes
- change shoes and socks at least once daily
- for athlete's foot and ringworm: use daily for 4 weeks
- for jock itch: use daily for 2 weeks
- if condition persists longer, consult a doctor
- this product is not effective on the scalp or nails

Other information

- store at 2° - 30° C (36° - 86° F)
- Lot No. & Exp. Date: see box or see crimp of tube

Inactive ingredients

cetostearyl alcohol, methylparaben, mineral oil, paraffin, polyoxyl 40 hydrogenated castor oil, polysorbate 80, water

Questions?

Call 1-833-IBN-SINA (1-833-426-7462)

Manufactured by:

The IBN SINA Pharmaceutical Industry Ltd.

Holding # A-80, Ward # 9, Shafipur, Kaliakoir

Gazipur-1751 Bangladesh

www.ibnsinapharma.com

Product of Bangladesh

PACKAGE LABEL

NDC 72103-525-10

Jock Itch Cream

Clotrimazole Cream, USP 1%

Antifungal Cream

Net Wt. 0.35 oz (10g)

Cures Most Jock Itch